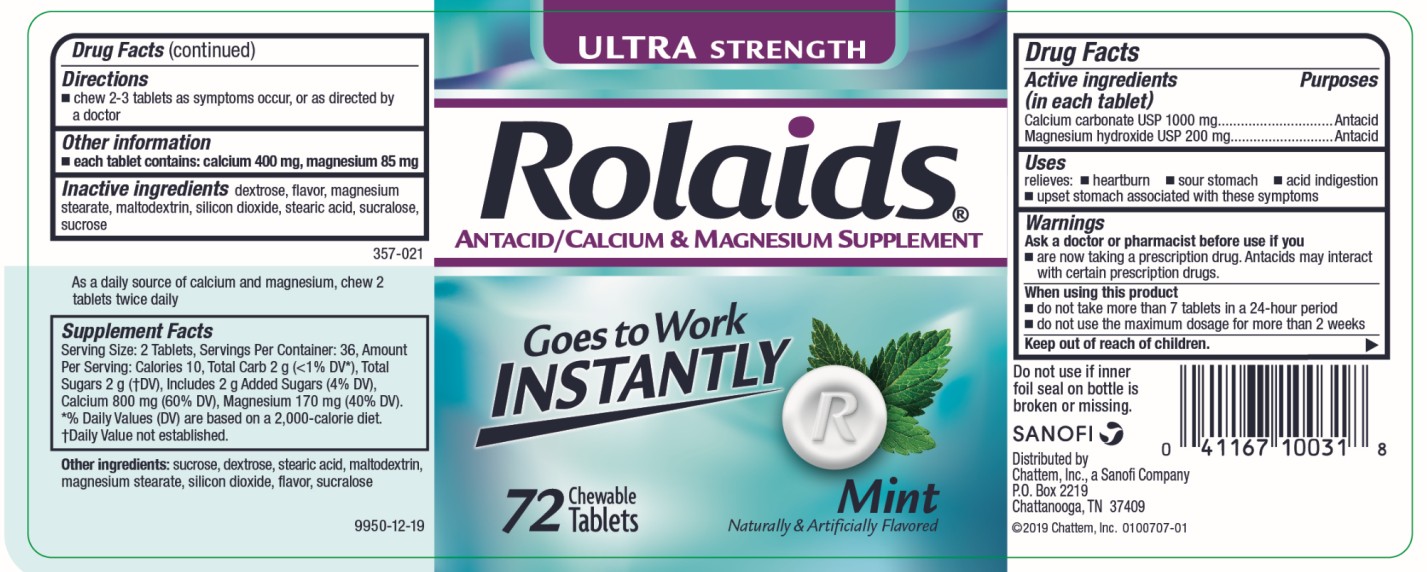 DRUG LABEL: Rolaids Ultra Strength Mint
NDC: 41167-1003 | Form: TABLET, CHEWABLE
Manufacturer: Chattem, Inc.
Category: otc | Type: HUMAN OTC DRUG LABEL
Date: 20260114

ACTIVE INGREDIENTS: CALCIUM CARBONATE 1000 mg/1 1; MAGNESIUM HYDROXIDE 200 mg/1 1
INACTIVE INGREDIENTS: DEXTROSE; MAGNESIUM STEARATE; SILICON DIOXIDE; STEARIC ACID; SUCRALOSE; SUCROSE

Rolaids Ultra Strength Tablets Mint

ULTRA Strength Antacid Rolaids Mint 72 Chewable Tablets

Drug Facts

Active ingredient

(in each tablet)
Calcium carbonate USP 1000 mg
Magnesium hydroxide USP 200 mg

Purpose

Antacid

Use

relieves:

- heartburn
- sour stomach
- acid indigestion

Warnings

Ask a doctor or pharmacist before use if you are

now taking a prescription drug. Antacids may interact with certain prescription drugs.

When using this product

- do not take more than 7 tablets in a 24-hour period
- do not use the maximum dosage for more than 2 weeks

Directions

- chew 2-3 tablets as symptoms occur, or as directed by a doctor

Other information

each tablet contains: calcium 400 mg, magnesium 85 mg

Inactive ingredients

dextrose, flavor, magnesium stearate, silicon dioxide, stearic acid, sucralose, sucrose (309-055)

As a daily source of calcium and magnesium, chew 2 tablets twice daily.

Supplement Facts
Serving Size: 2 Tablets, Servings Per Container: 36, Amount Per Serving: Calories 12, Total Carb 2 g (<1% DV*), Sugars 2 g (†DV), Calcium 800 mg (54% DV), Magnesium 170 mg (29% DV). *Percent Daily Values (DV) are based on a 2,000 calories diet.
†Daily Value not established.

Other ingredients

sucrose, dextrose, stearic acid, magnesium stearate, silicon dioxide, flavor, sucralose

PRINCIPAL DISPLAY PANEL

ULTRA STRENGTH
Rolaids®
ANTACID
Rapid Relief of:
Heartburn
Acid Indigestion
72 Chewable Tablets
Mint